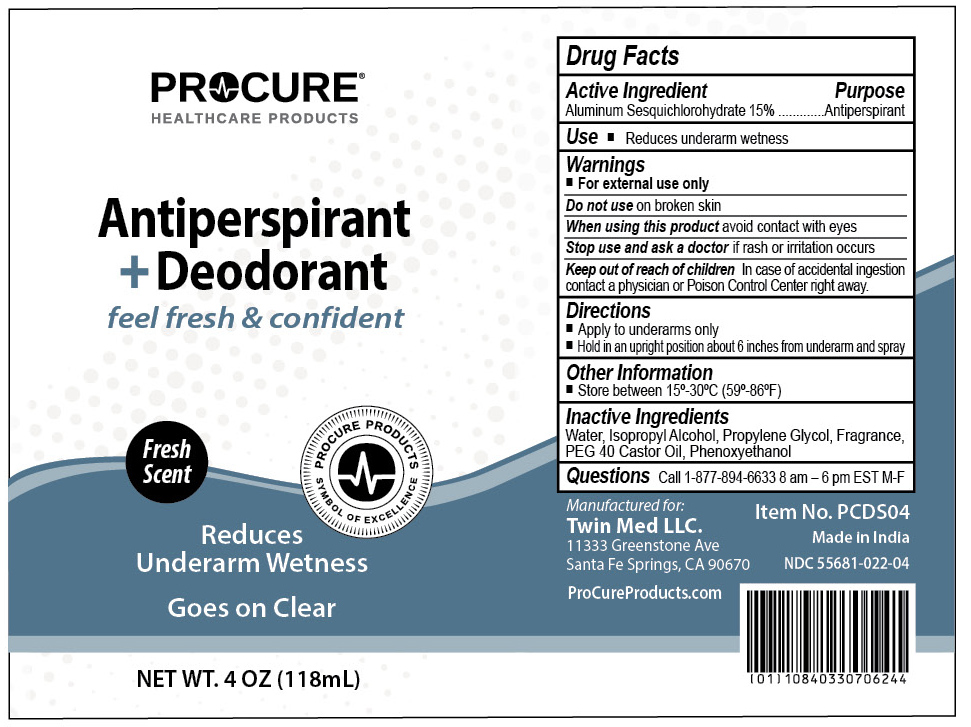 DRUG LABEL: ProCure Antiperspirant and Deodorant
NDC: 55681-022 | Form: SPRAY
Manufacturer: Twin Med LLC
Category: otc | Type: HUMAN OTC DRUG LABEL
Date: 20250713

ACTIVE INGREDIENTS: ALUMINUM SESQUICHLOROHYDRATE 15 g/100 mL
INACTIVE INGREDIENTS: ISOPROPYL ALCOHOL; PEG-40 CASTOR OIL; PHENOXYETHANOL; WATER

Active Ingredient

Aluminum Sesquichlorohydrate 15%

Purpose

Antiperspirant

Use

Use reduces underarm wetness

Warnings

For external use only

Do not use on broken skin

Stop use and ask a doctor if rash or irritation occurs

Ask a doctor before use if you have kidney disease

Keep out of reach of children. If swallowed, contact a physician or poison control center right away.

Directions

- Apply to underarms only
- Hold in an upright position about 6 inches from underarm and spray

Inactive Ingredients

Water, Isopropyl Alcohol, Propylene Glycol, Fragrance, PEG 40 Castor Oil, Phenoxyethanol